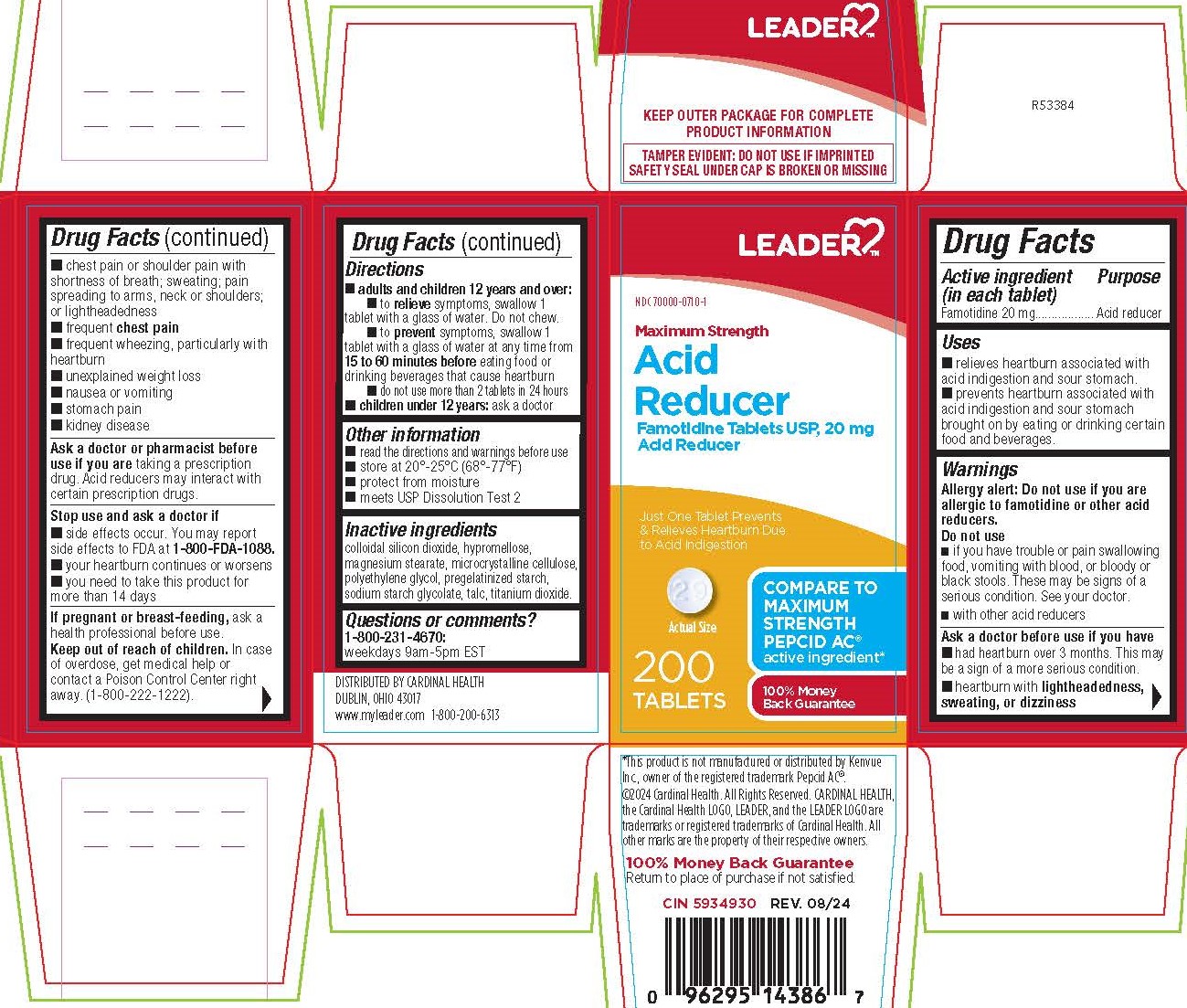 DRUG LABEL: Famotidine
NDC: 70000-0710 | Form: TABLET, FILM COATED
Manufacturer: LEADER/ Cardinal Health 110, Inc.
Category: otc | Type: HUMAN OTC DRUG LABEL
Date: 20250211

ACTIVE INGREDIENTS: FAMOTIDINE 20 mg/1 1
INACTIVE INGREDIENTS: POLYETHYLENE GLYCOL 400; MAGNESIUM STEARATE; MICROCRYSTALLINE CELLULOSE; HYPROMELLOSE 2910 (5 MPA.S); STARCH, CORN; TITANIUM DIOXIDE; TALC; SODIUM STARCH GLYCOLATE TYPE A; SILICON DIOXIDE

5688-Leader

Drug Facts

Active ingredient (in each tablet)
Famotidine 20 mg

Purpose
Acid reducer

Uses

- relieves heartburn associated with acid indigestion and sour stomach.
- prevents heartburn associated with acid indigestion and sour stomach brought on by eating or drinking certain food and beverages.

Allergy alert: Do not use if you are allergic to famotidine or other acid reducers.

Do not use

- if you have trouble or pain swallowing food, vomiting with blood, or bloody or black stools. These may be signs of a serious condition. See your doctor.
- with other acid reducers

Ask a doctor before use if you have

- had heartburn over 3 months. This may be a sign of a more serious condition.
- heartburn with lightheadedness, sweating, or dizziness
- chest pain or shoulder pain with shortness of breath; sweating; pain spreading to arms, neck or shoulders; or lightheadedness
- frequent chest pain
- frequent wheezing, particularly with heartburn
- unexplained weight loss
- nausea or vomiting
- stomach pain
- kidney disease

Ask a doctor or pharmacist before use if you are taking a prescription drug. Acid reducers may interact with certain prescription drugs.

Stop use and ask a doctor if

- side effects occur. You may report side effects to FDA at 1-800-FDA-1088.
- your heartburn continues or worsens
- you need to take this product for more than 14 days

PREGNANCY OR BREAST FEEDING

If pregnant or breast-feeding, ask a health professional before use.

Keep out of reach of children.

OVERDOSAGE

In case of overdose, get medical help or contact a Poison Control Center right away. (1-800-222-1222).

Directions

- adults and children 12 years and over:
- to relieve symptoms, swallow 1 tablet with a glass of water. Do not chew.
- to prevent symptoms, swallow 1 tablet with a glass of water at any time from 15 to 60 minutes before eating food or drinking beverages that cause heartburn
- do not use more than 2 tablets in 24 hours
- children under 12 years: ask a doctor

Other information

- read the directions and warnings before use
- store at 20°-25°C (68°-77°F)
- protect from moisture
- meets USP Dissolution Test 2

INACTIVE INGREDIENT

colloidal silicon dioxide, hypromellose, magnesium stearate, microcrystalline cellulose, polyethylene glycol, pregelatinized starch, sodium starch glycolate, talc, titanium dioxide.

Questions or comments?

1-800-231-4670:
weekdays 9am-5pm EST

DISTRIBUTED BY CARDINAL HEALTH
DUBLIN, OHIO 43017
www.myleader.com 1-800-200-6313

*This product is not manufactured or distributed by Kenvue Inc., owner of the registered trademark Pepcid AC®.

KEEP OUTER PACKAGE FOR COMPLETE PRODUCT INFORMATION

TAMPER EVIDENT: DO NOT USE IF IMPRINTED SAFETY SEAL UNDER CAP IS BROKEN OR MISSING

PACKAGE LABEL

NDC 70000-0710-1

Maximum Strength

Acid Reducer

Famotidine Tablets USP, 20 mg

Just One Tablet Prevents
& Relieves Heartburn Due
to Acid Indigestion

COMPARE TO MAXIMUM STRENGTH PEPCID AC® active ingredient*

200
TABLETS